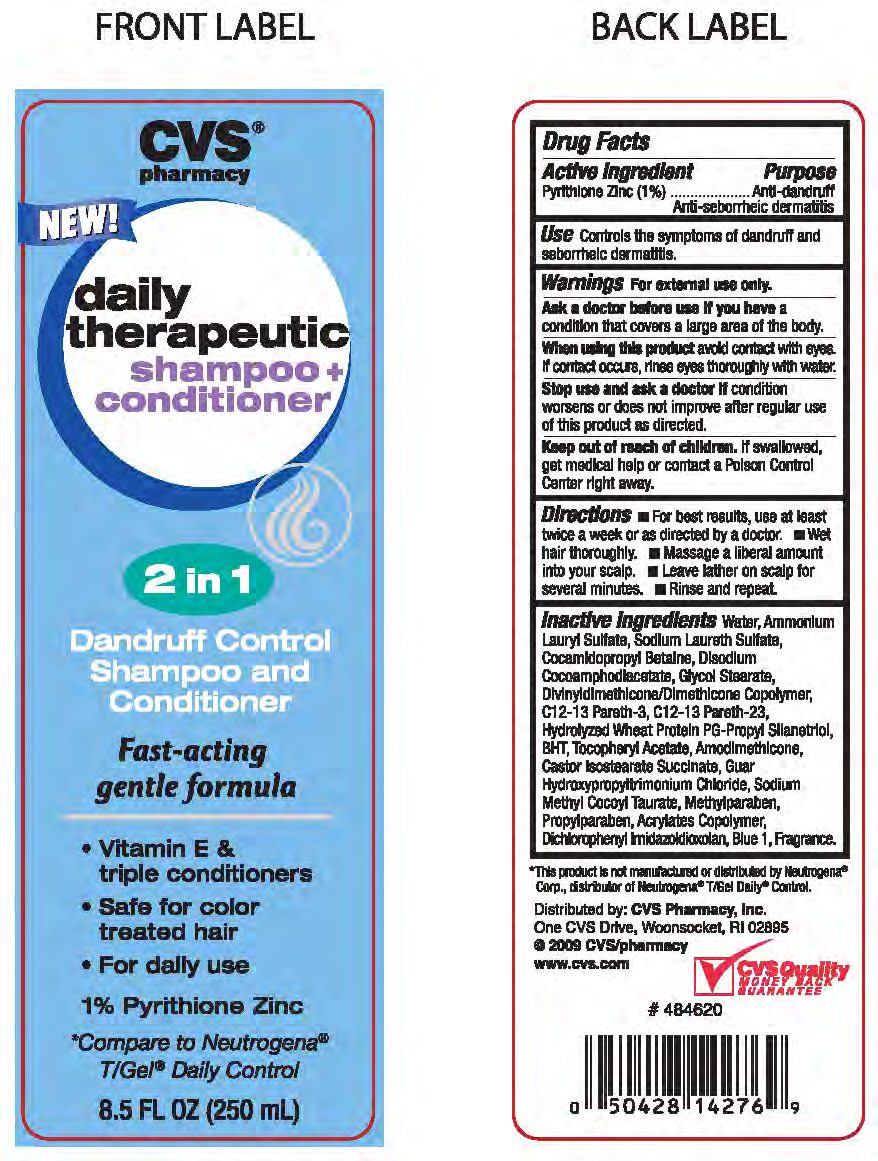 DRUG LABEL: PYRITHIONE ZINC
NDC: 59779-016 | Form: LIQUID
Manufacturer: CVS Pharmacy
Category: otc | Type: HUMAN OTC DRUG LABEL
Date: 20100716

ACTIVE INGREDIENTS: PYRITHIONE ZINC 29 mg/1 mL
INACTIVE INGREDIENTS: WATER; AMMONIUM LAURYL SULFATE; SODIUM LAURETH SULFATE; COCAMIDOPROPYL BETAINE; BUTYLATED HYDROXYTOLUENE; .ALPHA.-TOCOPHEROL ACETATE, D-; POLYOXYL 100 STEARATE; METHYLPARABEN; PROPYLPARABEN; COCAMIDOPROPYL BETAINE; CARBOMER 934; SODIUM LAURETH-2 SULFATE; DIMETHICONE; TRIMETHYL OCTADECYL AMMONIUM CHLORIDE; DIAZOLIDINYL UREA

drug facts

Active ingredient Purpose
Pyrithione Zinc (1%)..................................Anti-dandruff Anti-seborrheic dermatitis

Active ingredient Purpose
Pyrithione Zinc (1%)...............................Anti-dandruff Anti-seborrheic dermatitis
Use Controls the symptoms of dandruff and seborrheic dermatitis

Keep out of reach of children. If swallowed, get medical help
or contact a Poison Control Center right away.

INDICATIONS AND USAGE

Directions - for best results, use at least twice a week or as directed by a doctor.

- Wet hair thoroughly. - Massage a liberal amount into your scalp.

- Leave lather on scalp for several minutes - Rinse and repeat.

Warnings For external use only.
Ask a doctor before use if you have a condition that covers a large area of the body.
When using this product avoid contact with eyes. If contact occurs, rinse eyes thoroughly with water.
Stop use and ask a doctor if
condition worsens or does not improve after regular use of this product as directed.
Keep out of reach of children. If swallowed, get medical
help or contact a Poison Control Center right away.

DOSAGE AND ADMINISTRATION

Directions - for best results, use at least twice a week or as directed by a doctor.

- Wet hair thoroughly. - Massage a liberal amount into your scalp.

- Leave lather on scalp for several minutes - Rinse and repeat.

INACTIVE INGREDIENT

Inactive Ingredients Water, Ammonium Lauryl Sulfate, Sodium Laureth Sulfate,
Cocoamphodlacatate, Glycol Stearate, Divinyidimethicone.Dimethicone Copolymer,
C12-13 Pareth-3, C12-13 Pareth-23, Hydrolyzed Wheat Protein PG-Propyl Silanetriol,
BHT, Tocopharyl Acetate, Amodimethicone, Castor Isostearate Succinate,
Guar Hydroxypropyltrimonium Chloride, Sodium Methyl Cocoyl Tauratem,
Methylparaben, Propylparaben, Acrylates Copolymer, Dichlorophenyl Inidazoidioxoian,
Blue 1, Fragrance